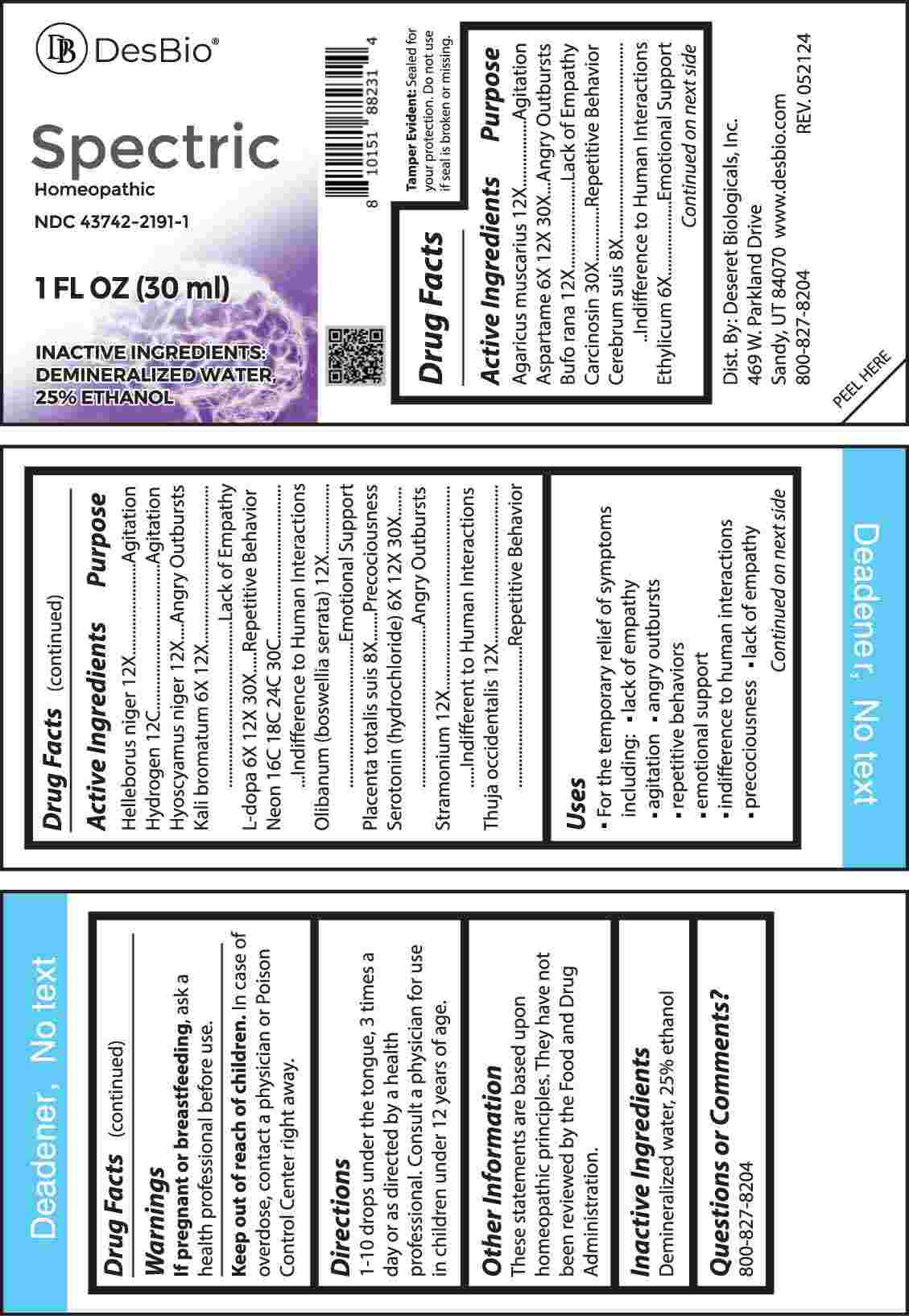 DRUG LABEL: Spectric
NDC: 43742-2191 | Form: LIQUID
Manufacturer: Deseret Biologicals, Inc
Category: homeopathic | Type: HUMAN OTC DRUG LABEL
Date: 20240923

ACTIVE INGREDIENTS: AMANITA MUSCARIA FRUITING BODY 12 [hp_X]/1 mL; ASPARTAME 6 [hp_X]/1 mL; BUFO BUFO CUTANEOUS GLAND 12 [hp_X]/1 mL; HUMAN BREAST TUMOR CELL 30 [hp_X]/1 mL; SUS SCROFA CEREBRUM 8 [hp_X]/1 mL; ALCOHOL 6 [hp_X]/1 mL; HELLEBORUS NIGER ROOT 12 [hp_X]/1 mL; HYDROGEN 12 [hp_C]/1 mL; HYOSCYAMUS NIGER 12 [hp_X]/1 mL; POTASSIUM BROMIDE 6 [hp_X]/1 mL; LEVODOPA 6 [hp_X]/1 mL; NEON 16 [hp_C]/1 mL; INDIAN FRANKINCENSE 12 [hp_X]/1 mL; SUS SCROFA PLACENTA 8 [hp_X]/1 mL; SEROTONIN HYDROCHLORIDE 6 [hp_X]/1 mL; DATURA STRAMONIUM 12 [hp_X]/1 mL; THUJA OCCIDENTALIS LEAFY TWIG 12 [hp_X]/1 mL
INACTIVE INGREDIENTS: WATER

DRUG FACTS:

ACTIVE INGREDIENTS:

Agaricus Muscarius 12X, Aspartame 6X, 12X, 30X, Bufo Rana 12X, Carcinosin 30X, Cerebrum Suis 8X, Ethylicum 6X, Helleborus Niger 12X, Hydrogen 12C, Hyoscyamus Niger 12X, Kali Bromatum 6X, 12X, L-Dopa 6X, 12X, 30X, Neon 16C, 18C, 24C, 30C, Olibanum (Boswellia Serrata) 12X, Placenta Totalis Suis 8X, Serotonin (Hydrochloride) 6X, 12X, 30X, Stramonium 12X, Thuja Occidentalis 12X.

PURPOSE:

Agaricus Muscarius - Agitation, Aspartame – Angry Outbursts, Bufo Rana – Lack of Empathy, Carcinosin – Repetitive Behavior, Cerebrum Suis – Indifference to Human Interactions, Ethylicum – Emotional Support, Helleborus Niger - Agitation, Hydrogen - Agitation, Hyoscyamus Niger – Angry Outbursts, Kali Bromatum – Lack of Empathy, L-Dopa – Repetitive Behavior, Neon – Indifference to Human Interactions, Olibanum (Boswellia Serrata) – Emotional Support, Placenta Totalis Suis - Precociousness, Serotonin (Hydrochloride) – Angry Outbursts, Stramonium – Indifferent to Human Interactions, Thuja Occidentalis – Repetitive Behavior

USES:

• For the temporary relief of symptoms including:

• lack of empathy • agitation • angry outburst • repetitive behaviors

• emotional support • indifferent to human interaction • precociousness

These statements are based upon homeopathic principles. They have not been reviewed by the Food and Drug Administration.

WARNINGS:

If pregnant or breast-feeding, ask a health professional before use.

Keep out of reach of children. In case of overdose, contact a physician or Poison Control Center right away.

Tamper Evident: Sealed for your protection. Do not use if seal is broken or missing.

KEEP OUT OF REACH OF CHILDREN:

In case of overdose, contact a physician or Poison Control Center right away.

DIRECTIONS:

1-10 drops under the tongue, 3 times a day or as directed by a health professional. Consult a physician for use in children under 12 years of age.

INACTIVE INGREDIENTS:

Demineralized water, 25% ethanol

QUESTIONS:

Dist. By: Deseret Biologicals, Inc.
469 W. Parkland Drive
Sandy, UT 84070

www.desbio.com

800-827-8204

PACKAGE LABEL DISPLAY:

DesBio

Spectric

Homeopathic

NDC 43742-2191-1

1 FL OZ (30ml)